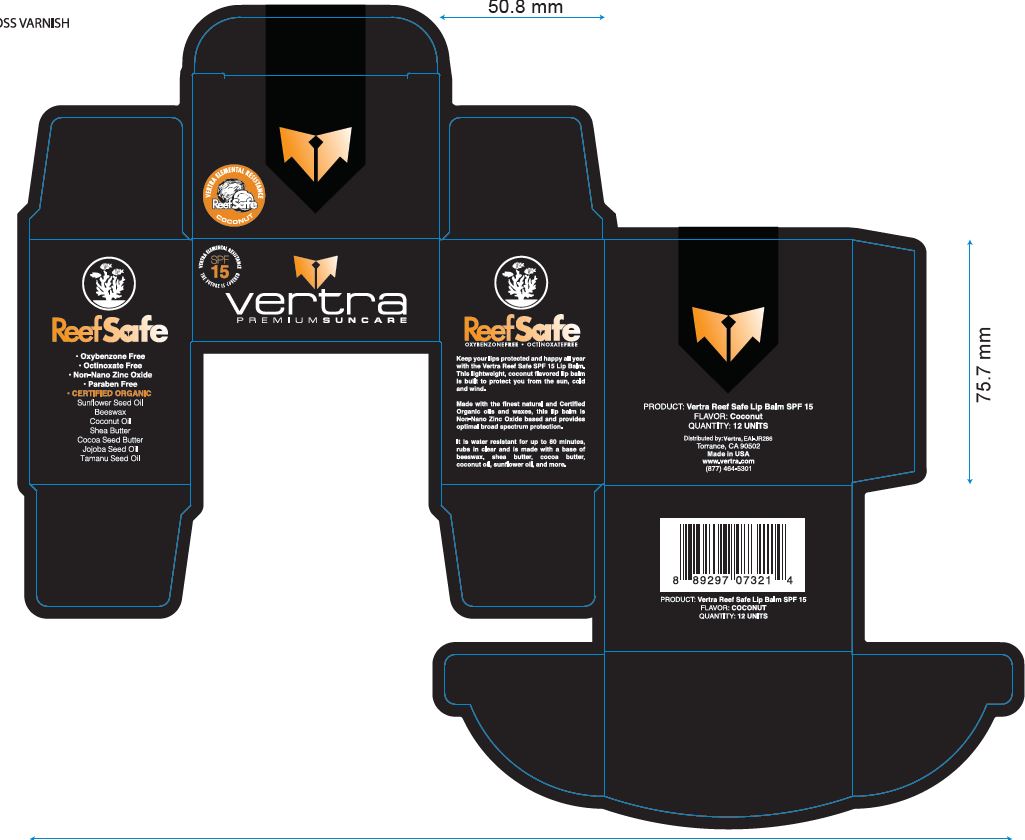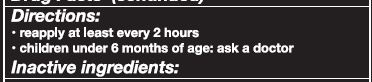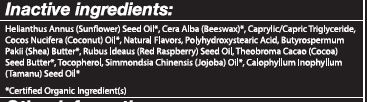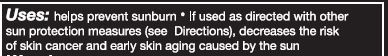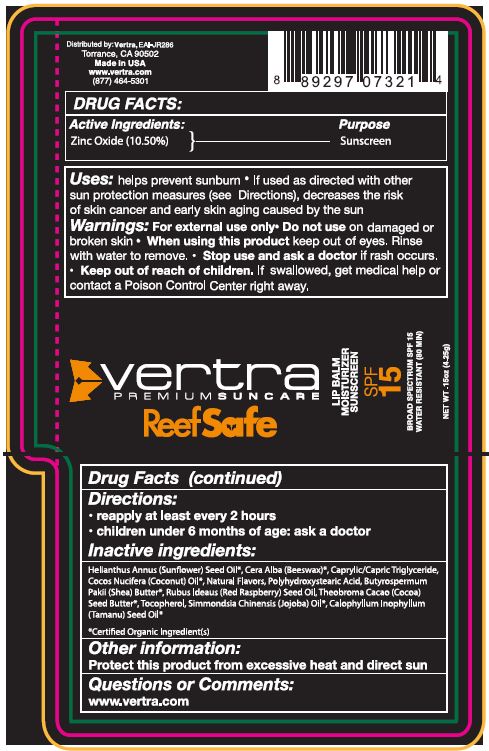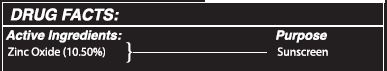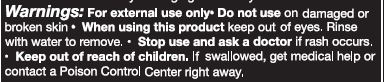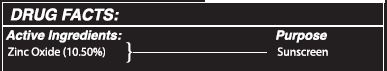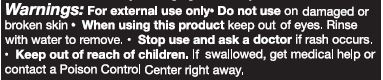 DRUG LABEL: SUNSCREEN
NDC: 62932-217 | Form: STICK
Manufacturer: Private Label Select Ltd CO
Category: otc | Type: HUMAN OTC DRUG LABEL
Date: 20200401

ACTIVE INGREDIENTS: ZINC OXIDE 10.5 g/100 g
INACTIVE INGREDIENTS: MEDIUM-CHAIN TRIGLYCERIDES; SHEA BUTTER; TAMANU OIL; COCOA BUTTER; COCONUT OIL; JOJOBA OIL; WHITE WAX; SUNFLOWER OIL; POLYHYDROXYSTEARIC ACID (2300 MW); TOCOPHEROL; RASPBERRY SEED OIL

Vertra Lip Balm Moisturizing Sunscreen, SPF 15